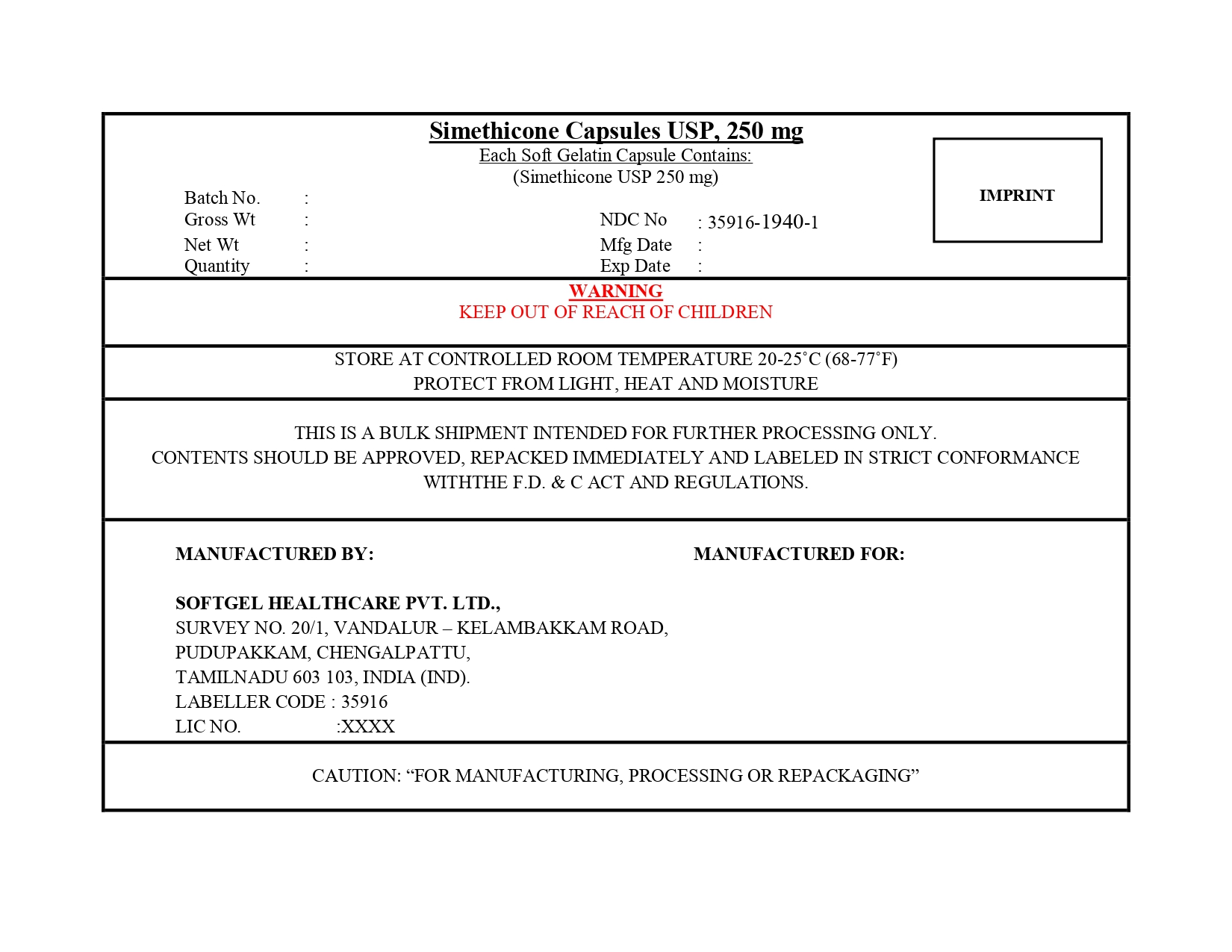 DRUG LABEL: Simethicone
NDC: 35916-1940 | Form: CAPSULE, LIQUID FILLED
Manufacturer: SOFTGEL HEALTHCARE PRIVATE LIMITED
Category: otc | Type: HUMAN OTC DRUG LABEL
Date: 20260128

ACTIVE INGREDIENTS: DIMETHICONE 250 mg/1 1
INACTIVE INGREDIENTS: WATER; GELATIN; D&C RED NO. 33; FD&C BLUE NO. 1; GLYCERIN; SILICON DIOXIDE

Simethicone Capsules USP, 250 mg

Active ingredient (in each softgel)

Simethicone USP 250 mg

Purpose

Antigas

Use

for the relief of

- pressure, bloating, and fullness commonly referred to as gas

Warnings

Keep out of reach of children.

Directions

- adults and children 12 years and older: swallow with water 1 or 2 softgels as needed after meals and at bedtime
- do not exceed 2 softgels in 24 hours except under the advice and supervision of a physician

Other information

- store at controlled room temperature 20-25ºC (68-77ºF)
- protect from light, heat, and moisture

Inactive ingredients

D&C red no.33, FD&C blue no.1, gelatin, glycerin, purified water

Principal Display Panel

NDC 35916-1940-2

Compare to Gas-X® Maximum Strength Active Ingredient*

Simethicone Capsules USP, 250 mg

Simethicone 250 mg / Antigas (Relieves Gas Fast)

RELIEVES GAS FAST:

- Pressure
- Bloating
- Discomfort

50 Softgels